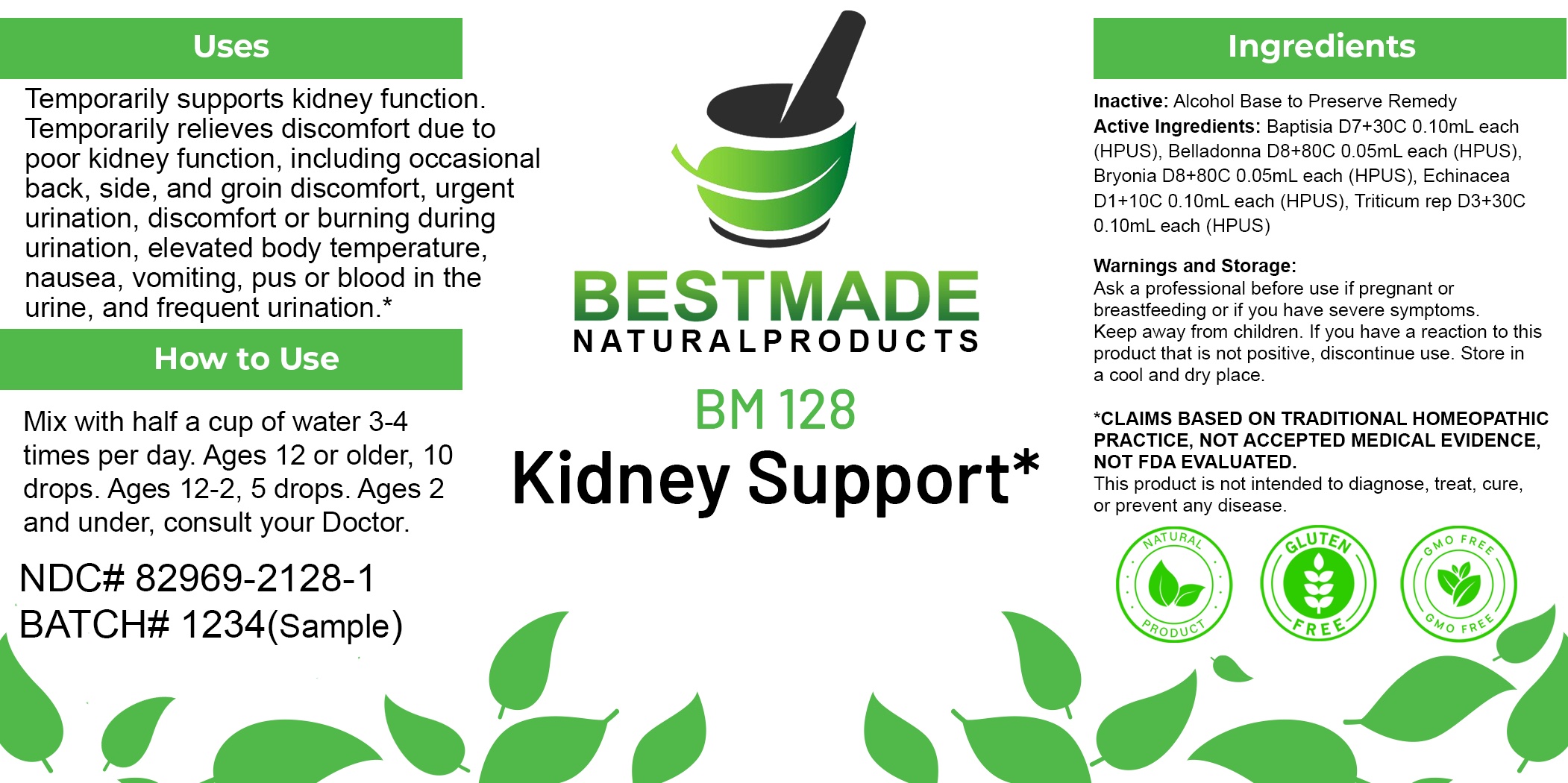 DRUG LABEL: Bestmade Natural Products BM128
NDC: 82969-2128 | Form: LIQUID
Manufacturer: Bestmade Natural Products
Category: homeopathic | Type: HUMAN OTC DRUG LABEL
Date: 20250210

ACTIVE INGREDIENTS: BRYONIA ALBA ROOT 30 [hp_C]/30 [hp_C]; BAPTISIA TINCTORIA ROOT 30 [hp_C]/30 [hp_C]; ATROPA BELLADONNA 30 [hp_C]/30 [hp_C]; ECHINACEA ANGUSTIFOLIA WHOLE 30 [hp_C]/30 [hp_C]; ELYMUS REPENS ROOT 30 [hp_C]/30 [hp_C]
INACTIVE INGREDIENTS: ALCOHOL 30 [hp_C]/30 [hp_C]

BM128

DOSAGE AND ADMINISTRATION

How to Use

Mix with half a cup of water 3-4 times per day. Ages 12 or older, 10 drops. Ages 12-2, 5 drops. Ages 2 and under, consult your Doctor.

Inactive:

Alcohol Base to Preserve Product

ACTIVE INGREDIENTS

Baptisia D7+30C 0.10mL each (HPUS), Belladonna D8+80C 0.05mL each (HPUS), Bryonia D8+80C 0.05mL each (HPUS), Echinacea D1+10C 0.10mL each (HPUS), Triticum rep D3+30C 0.10mL each (HPUS)

Uses
Temporarily supports kidney function. Temporarily relieves discomfort due to poor kidney function, including occasional back, side, and groin discomfort, urgent urination, discomfort or burning during urination, elevated body temperature, nausea, vomiting, pus or blood in the urine, and frequent urination.*

KEEP OUT OF REACH OF CHILDREN

Warnings and Storage:

Ask a professional before use if pregnant or breastfeeding or if you have severe symptoms.

Keep away from children. If you have a reaction to this product that is not positive, discontinue use. Store in a cool and dry place

*CLAIMS BASED ON TRADITIONAL HOMEOPATHIC PRACTICE, NOT ACCEPTED MEDICAL EVIDENCE NOT FDA EVALUATED.
This product is not intended to diagnose, treat, cure, or prevent any disease.

Uses
Temporarily supports kidney function. Temporarily relieves discomfort due to poor kidney function, including occasional back, side, and groin discomfort, urgent urination, discomfort or burning during urination, elevated body temperature, nausea, vomiting, pus or blood in the urine, and frequent urination.*

Warnings and Storage:

Ask a professional before use if pregnant or breastfeeding or if you have severe symptoms.

Keep away from children. If you have a reaction to this product that is not positive, discontinue use. Store in a cool and dry place

*CLAIMS BASED ON TRADITIONAL HOMEOPATHIC PRACTICE, NOT ACCEPTED MEDICAL EVIDENCE NOT FDA EVALUATED.
This product is not intended to diagnose, treat, cure, or prevent any disease.

Entire package label